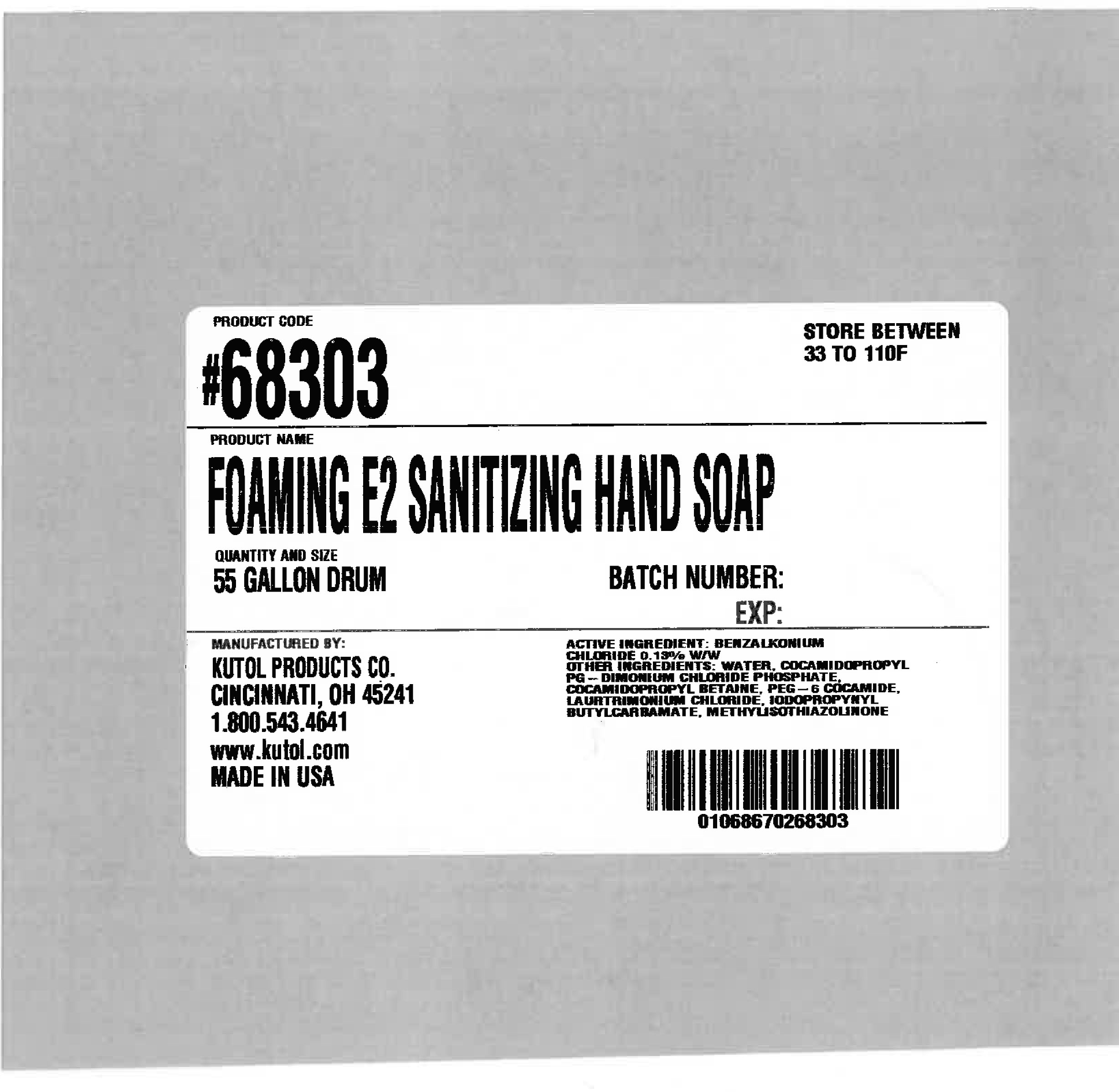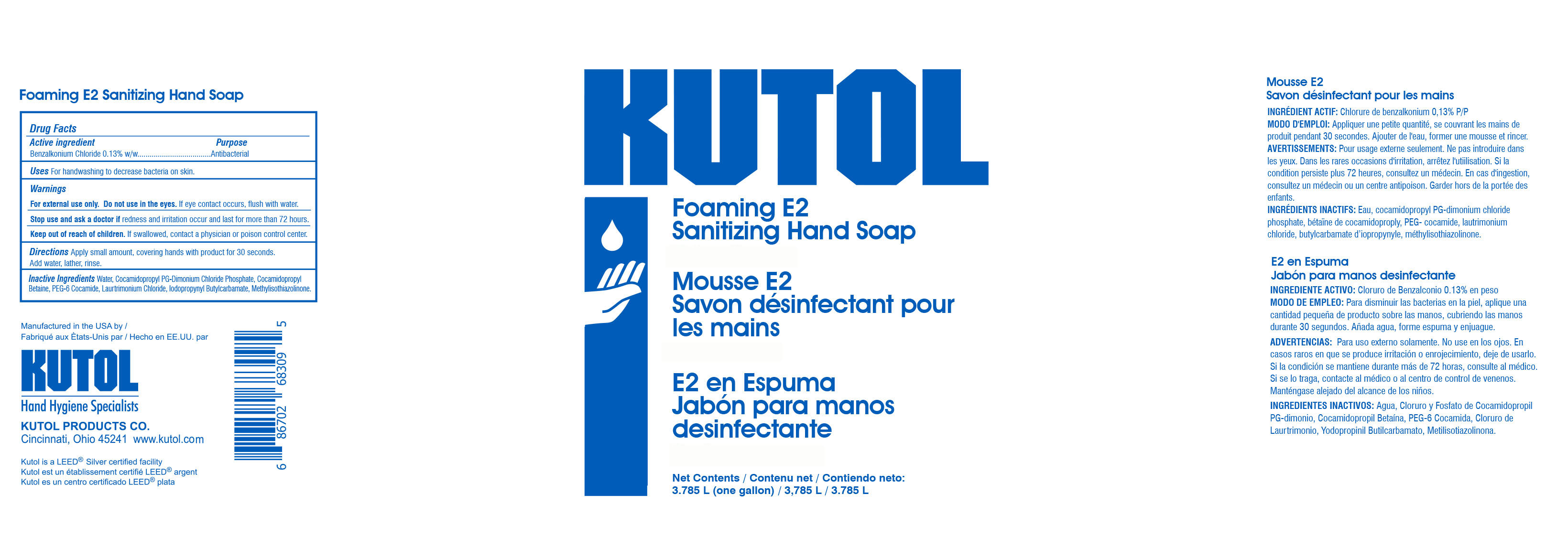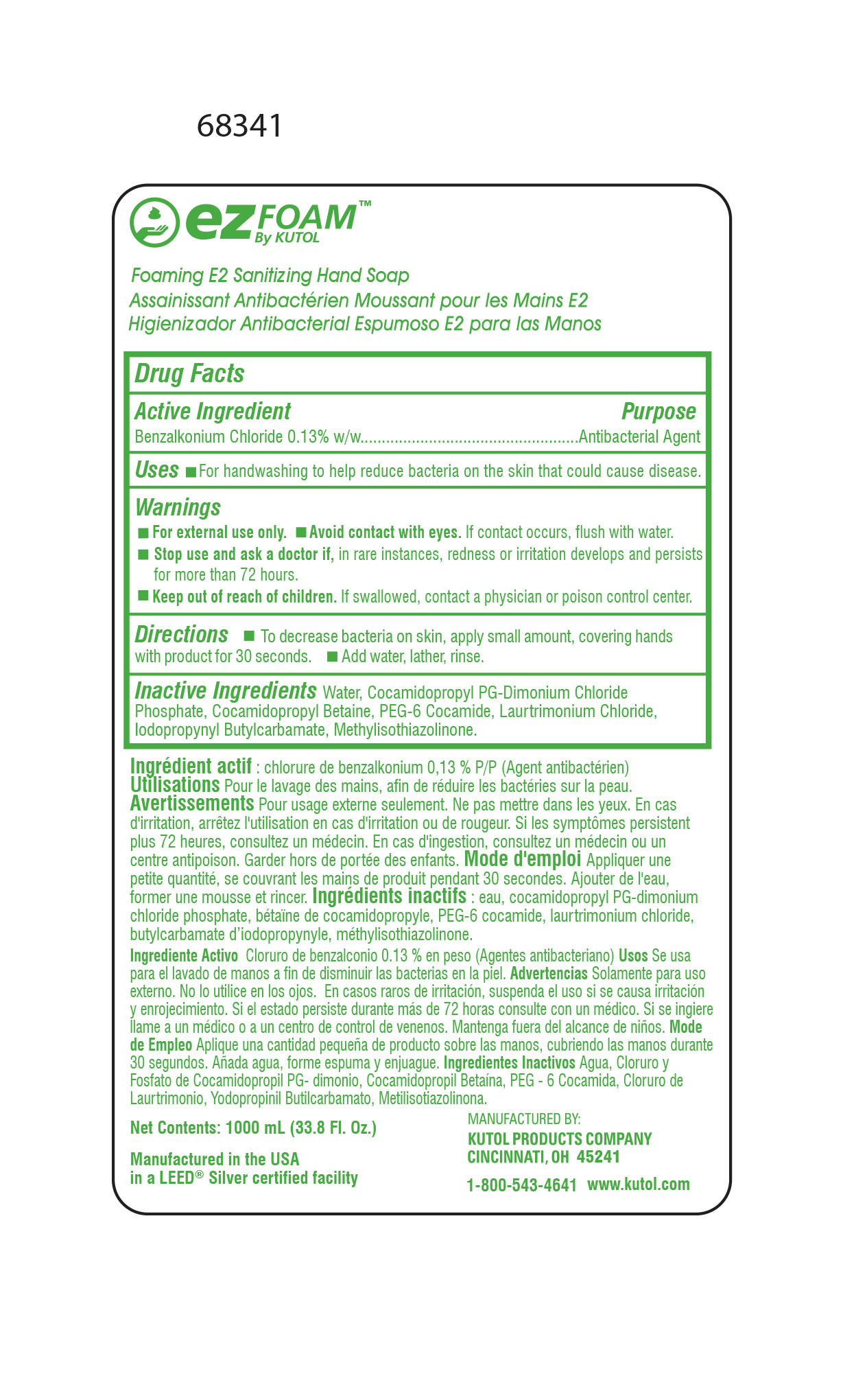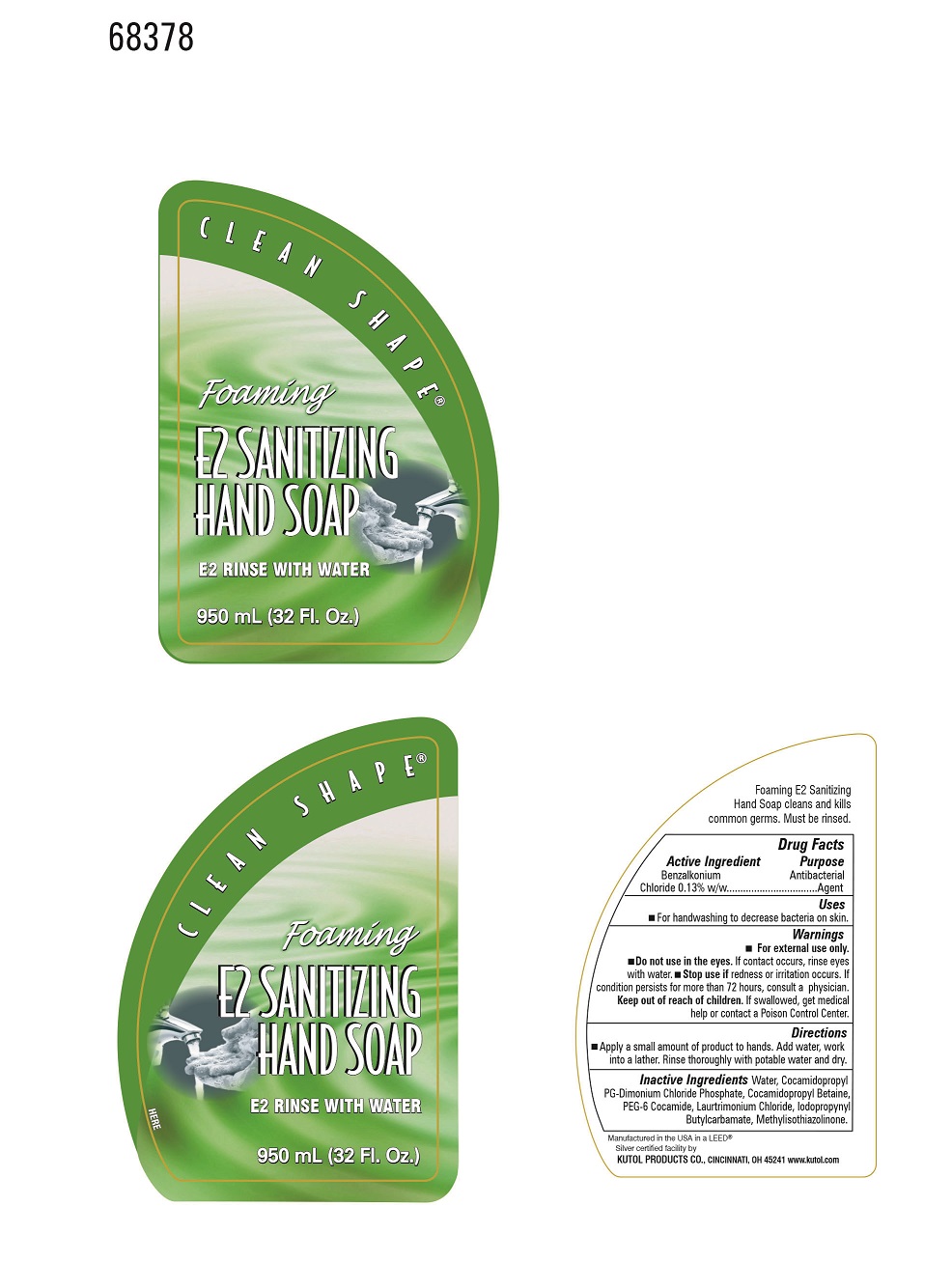 DRUG LABEL: Foaming Sanitizing Hand
NDC: 50865-683 | Form: SOAP
Manufacturer: Kutol Products Company
Category: otc | Type: HUMAN OTC DRUG LABEL
Date: 20241218

ACTIVE INGREDIENTS: BENZALKONIUM CHLORIDE 0.003 mg/1 mL
INACTIVE INGREDIENTS: WATER; COCAMIDOPROPYL BETAINE; COCAMIDOPROPYL PG-DIMONIUM CHLORIDE PHOSPHATE; PEG-6 COCAMIDE; LAURTRIMONIUM CHLORIDE; METHYLISOTHIAZOLINONE; IODOPROPYNYL BUTYLCARBAMATE

F683F Foaming sanitizing soap

Active Ingredient

Benzalkonium Chloride 0.13% w/w

Purpose

Antibacterial

Keep out of reach of children. If swallowed, contact a physician or poison control center.

INDICATIONS AND USAGE

Uses For handwashing to decrease bacteria on skin

DOSAGE AND ADMINISTRATION

Directions Apply small amount, covering hands with product for 30 seconds. Add water, lather, rinse.

Warnings

For external use only. Do not use in the eyes. If eye contact occurs, flush eyes with water.

Stop use and ask a doctor if redness and irritation occur and last for more than 72 hours.

Inactive Ingredients

water, cocamidopropyl PG-dimonium chloride phosphate,cocamidopropyl betaine, PEG-6 cocamide, laurtrimonium chloride, iodopropynyl butylcarbamate,methylisothiazolinone.